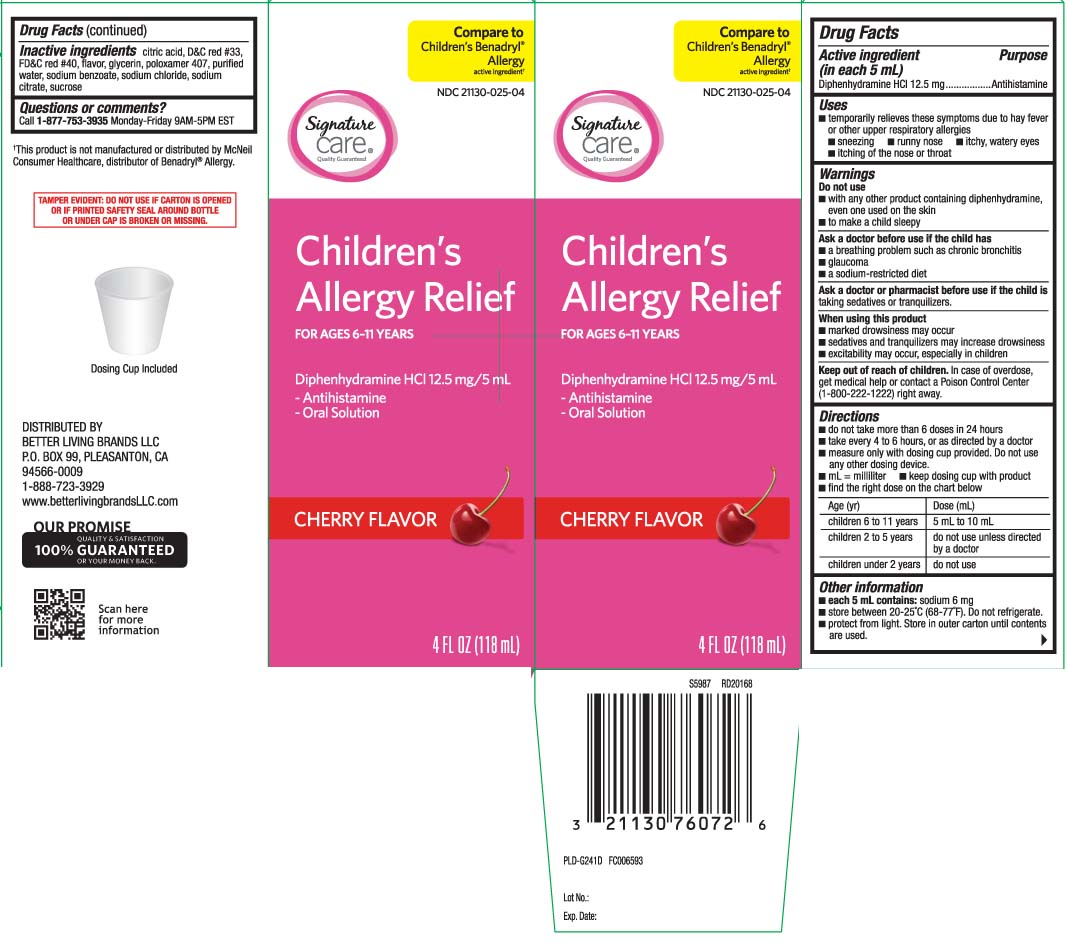 DRUG LABEL: Childrens Allergy
NDC: 21130-025 | Form: LIQUID
Manufacturer: Safeway, Inc.
Category: otc | Type: HUMAN OTC DRUG LABEL
Date: 20250508

ACTIVE INGREDIENTS: DIPHENHYDRAMINE HYDROCHLORIDE 12.5 mg/5 mL
INACTIVE INGREDIENTS: ANHYDROUS CITRIC ACID; GLYCERIN; POLOXAMER 407; WATER; SODIUM BENZOATE; SODIUM CHLORIDE; TRISODIUM CITRATE DIHYDRATE; SUCROSE; D&C RED NO. 33; FD&C RED NO. 40

Childrens Allergy

Active ingredient (in each 5 mL)

Diphenhydramine HCl 12.5 mg

Purpose

Antihistamine

Uses

- temporarily relieves these symptoms due to hay fever or other upper respiratory allergies:
  - runny nose
  - sneezing
  - itchy, watery eyes
  - itching of the nose or throat

Warnings

Do not use

- to make a child sleepy
- with any other product containing diphenhydramine, even one used on skin

Ask a doctor before use if the child has

- glaucoma
- a breathing problem such as chronic bronchitis
- a sodium-restricted diet

Ask a doctor or pharmacist before use if the child is

taking sedatives or tranquilizers.

When using this product

- marked drowsiness may occur
- sedatives and tranquilizers may increase drowsiness
- excitability may occur, especially in children

Keep out of the reach of children.

In case of overdose, get medical help or contact a Poison Control Center (1-800-222-1222) right away.

Directions

- do not take more than 6 doses in 24 hours
- take every 4 to 6 hours, or as directed by a doctor
- measure only with dosing cup provided. Do not use any other dosing device
- mL = milliliter
- keep dosing cup with product
- find the right dose on the chart below

age (yr) | dose (mL)
children 6 to 11 years | 5 mL to 10 m
children 2 to 5 years | do not use unless directed by a doctor
children under 2 years | do not use

Other information

- each 5 mL contain: sodium 6 mg
- store between 20-25ºC (68-77ºF). Do not refrigerate.
- protect from light. Store in outer carton until contents are used

Inactive ingredients

anhydrous citric acid, D&C red #33, FD&C red #40 flavor glycerin, poloxamer 407, purified water, sodium benzoate, sodium chloride, sodium citrate, sucrose

Questions or comments?

Call 1-888-723-3929 Monday-Friday 7AM-6PMPST

Principal Display Panel

FOR AGES 6-11 YEARS

Children's Allergy Relief

Diphenhydramine HCl 12.5 mg - Antihistamine

CHERRY FLAVOR

Compare toChildren's Benadryl® Allergy active ingredient*

- Relief of: Runny nose, sneezing, itching of the nose or throat & itchy, watery eyes
- Alcohol free
- Dosing cup included

FL OZ (mL)

*This product is not manufactured or distributed by McNeil Consumer Healthcare, distributors of Children's Benadryl® Allergy.

TAMPER EVIDENT: DO NOT USE IF CARTON IS OPENED OR IF PRINTED SAFETY SEAL AROUND BOTTLE OR UNDER THE CAP IS BROKEN OR MISSING.

DISTRIBUTED BY

BETTER LIVING BRANDS LLC

P.O. BOX 99, PLEASANTON, CA 94566-0009

www.betterlivingbrandsLLC.com